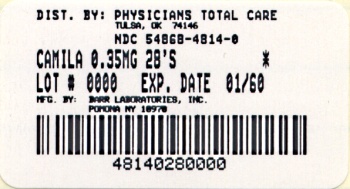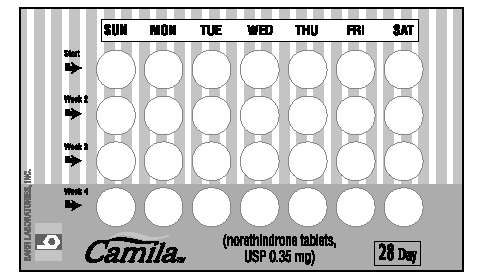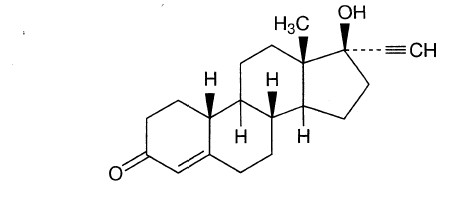 DRUG LABEL: Camila
NDC: 54868-4814 | Form: TABLET
Manufacturer: Physicians Total Care, Inc.
Category: prescription | Type: HUMAN PRESCRIPTION DRUG LABEL
Date: 20101202

ACTIVE INGREDIENTS: NORETHINDRONE 0.35 mg/1 1
INACTIVE INGREDIENTS: STARCH, CORN; FD&C RED NO. 40; LACTOSE MONOHYDRATE; MAGNESIUM STEARATE; POVIDONE; SODIUM STARCH GLYCOLATE TYPE A POTATO

Revised AUGUST 2002
1007150102

Rx only

Patients should be counseled that this product does not protect against HIV infection (AIDS) and other sexually transmitted diseases.

DESCRIPTION

Each light pink norethindrone tablet provides a continuous oral contraceptive regimen of 0.35 mg norethindrone daily, and has the following inactive ingredients: corn starch, FD&C red no. 40 aluminum lake, lactose monohydrate, magnesium stearate, povidone, and sodium starch glycolate.

The chemical name for norethindrone is 17-Hydroxy-19-Nor-17α-pregn-4-en-20-yn-3-one. The structural formula follows:

Norethindrone Therapeutic class=oral contraceptive

CLINICAL PHARMACOLOGY

1. Mode of Action:

Progestin-only oral contraceptives prevent conception by suppressing ovulation in approximately half of users, thickening the cervical mucus to inhibit sperm penetration, lowering the midcycle LH and FSH peaks, slowing the movement of the ovum through the fallopian tubes, and altering the endometrium.

2. Pharmacokinetics:

Serum progestin levels peak about two hours after oral administration, followed by rapid distribution and elimination. By 24 hours after drug ingestion, serum levels are near baseline, making efficacy dependent upon rigid adherence to the dosing schedule. There are large variations in serum levels among individual users. Progestin-only administration results in lower steady-state serum progestin levels and a shorter elimination half-life than concomitant administration with estrogens.

INDICATIONS AND USAGE

1. Indications:

Progestin-only oral contraceptives are indicated for the prevention of pregnancy.

2. Efficacy:

If used perfectly, the first-year failure rate for progestin-only oral contraceptives is 0.5%. However, the typical failure rate is estimated to be closer to 5%, due to late or omitted pills. The following table lists the pregnancy rates for users of all major methods of contraception.

Table 1 Comparison of reversible contraceptive methods: Percent of women experiencing a contraceptive failure (pregnancy) during the first year of use.
 | Percent of women experiencing; a pregnancy within the first year of use
Method | Average Use | Perfect Use
No contraception | 85 | 85
Spermicides | 21 | 6
Periodic abstinence | 20 | 1-9†
Withdrawal | 19 | 4
Cervical caps Given birth Never given birth | 36 18 | 26 9
Diaphragms | 18 | 6
Condoms Female Male | 21 12 | 5 3
Pills Progestin-only Combined | 3 | 0.5 0.1
IUDs Progesterone Copper T 380A | 2 0.8 | 1.5 0.6
Injectables | 0.3 | 0.3
Implant | 0.09 | 0.09

Adapted with permission.**Hatcher RA, Trussel J, Stewart F, Stewart GK, Kowal D, Guest F, Cates W, Pollcar M. Contraceptive Technology 1994-1996. New York, NY: Irvington Publishers. 1994.†Depending on method (calendar, ovulation, symptom-thermal, post-ovulation).

CONTRAINDICATIONS

Progestin-only oral contraceptives should not be used by women who currently have the following conditions:

- Known or suspected pregnancy
- Known or suspected carcinoma of the breast
- Undiagnosed abnormal genital bleeding
- Hypersensitivity to any component of this product
- Benign or malignant liver tumors
- Acute liver disease

WARNINGS

Cigarette smoking greatly increases the possibility of suffering heart attacks and strokes. Women who use oral contraceptives are strongly advised not to smoke.

Norethindrone Tablets do not contain estrogen and, therefore, this insert does not discuss the serious health risks that have been associated with the estrogen component of combined oral contraceptives. The healthcare provider is referred to the prescribing information of combined oral contraceptives for a discussion of those risks, including, but not limited to, an increased risk of serious cardiovascular disease in women who smoke, carcinoma of the breast and reproductive organs, hepatic neoplasia, and changes in carbohydrate and lipid metabolism. The relationship between progestin-only oral contraceptives and these risks have not been established and there are no studies definitely linking progestin-only pill (POP) use to an increased risk of heart attack or stroke.

The physician should remain alert to the earliest manifestation of symptoms of any serious disease and discontinue oral contraceptive therapy when appropriate.

1. Ectopic Pregnancy

The incidence of ectopic pregnancies for progestin-only oral contraceptive users is 5 per 1000 woman-years. Up to 10% of pregnancies reported in clinical studies of progestin-only oral contraceptive users are extrauterine. Although symptoms of ectopic pregnancy should be watched for, a history of ectopic pregnancy need not be considered a contraindication to use of this contraceptive method. Health providers should be alert to the possibility of an ectopic pregnancy in women who become pregnant or complain of lower abdominal pain while on progestin-only oral contraceptives.

2. Delayed Follicular Atresia/Ovarian Cysts:

If follicular development occurs, atresia of the follicle is sometimes delayed, and the follicle may continue to grow beyond the size it would attain in a normal cycle. Generally these enlarged follicles disappear spontaneously. Often they are asymptomatic; in some cases they are associated with mild abdominal pain. Rarely they may twist or rupture, requiring surgical intervention.

3. Irregular Genital Bleeding:

Irregular menstrual patterns are common among women using progestin-only oral contraceptives. If genital bleeding is suggestive of infection, malignancy or other abnormal conditions, such nonpharmacologic causes should be ruled out. If prolonged amenorrhea occurs, the possibility of pregnancy should be evaluated.

4. Carcinoma of the Breast and Reproductive Organs:

Some epidemiologic studies of oral contraceptive users have reported an increased relative risk of developing breast cancer, particularly at a younger age and apparently related to duration of use. These studies have predominantly involved combined oral contraceptives and there is insufficient data to determine whether the use of POPs similarly increases the risk. Women with breast cancer should not use oral contraceptives because the role of female hormones in breast cancer has not been fully determined.

Some studies suggest that oral contraceptive use has been associated with an increase in the risk of cervical intraepithelial neoplasia in some populations of women. However, there continues to be controversy about the extent to which such findings may be due to differences in sexual behavior and other factors. There is insufficient data to determine whether the use of POPs increases the risk of developing cervical intraepithelial neoplasia.

5. Hepatic Neoplasia:

Benign hepatic adenomas are associated with combined oral contraceptive use, although the incidence of benign tumors is rare in the United States. Rupture of benign, hepatic adenomas may cause death through intraabdominal hemorrhage

Studies from Britain and the U.S. have shown an increased risk of developing hepatocellular carcinoma in combined oral contraceptive users. However, these cancers are rare. There is insufficient data to determine whether POPs increase the risk of developing hepatic neoplasia.

PRECAUTIONS

1. General:

Patients should be counseled that this product does not protect against HIV infection (AIDS) and other sexually transmitted diseases.

2. Physical Examination and Follow-up:

It is considered good medical practice for sexually active women using oral contraceptives to have annual history and physical examinations. The physical examination may be deferred until after initiation of oral contraceptives if requested by the woman and judged appropriate by the clinician.

3. Carbohydrate and Lipid Metabolism:

Some users may experience slight deterioration in glucose tolerance, with increases in plasma insulin but women with diabetes mellitus who use progestin-only oral contraceptives do not generally experience changes in their insulin requirements. Nonetheless, prediabetic and diabetic women in particular should be carefully monitored while taking POPs.

Lipid metabolism is occasionally affected in that HDL, HDL2, and apolipoprotein A-I and A-II may be decreased; hepatic lipase may be increased. There is no effect on total cholesterol, HDL3, LDL, or VLDL.

4. Drug Interactions:

The effectiveness of progestin-only pills is reduced by hepatic enzyme-inducing drugs such as the anticonvulsants phenytoin, carbamazepine, and barbiturates, and the anti-tuberculosis drug rifampin. No significant interaction has been found with broad-spectrum antibiotics.

5. Interactions with Laboratory Tests:

The following endocrine tests may be affected by progestin-only oral contraceptive use

- Sex hormone-binding globulin (SHBG) concentrations may be decreased.
- Thyroxine concentrations may be decreased, due to a decrease in thyroid binding globulin (TBG).

6. Carcinogenesis:

See WARNINGS section.

7. Pregnancy:

Many studies have found no effects on fetal development associated with long-term use of contraceptive doses of oral progestins. The few studies of infant growth and development that have been conducted have not demonstrated significant adverse effects. It is nonetheless prudent to rule out suspected pregnancy before initiating any hormonal contraceptive use.

8. Nursing Mothers:

No adverse effects have been found on breastfeeding performance or on the health, growth or development of the infant. Small amounts of progestin pass into the breast milk, resulting in steroid levels in infant plasma of 1-6% of the levels of maternal plasma.

9. Fertility Following Discontinuation:

The limited available data indicate a rapid return of normal ovulation and fertility following discontinuation of progestin-only oral contraceptives.

10. Headache:

The onset or exacerbation of migraine or the development of severe headache with focal neurological symptoms which is recurrent or persistent requires discontinuation of progestin-only contraceptives and evaluation of the cause.

11. Pediatric Use:

Safety and efficacy of norethindrone have been established in women of reproductive age. Safety and efficacy are expected to be the same for postpubertal adolescents under the age of 16 and for users 16 years and older. Use of this product before menarche is not indicated.

INFORMATION FOR THE PATIENT

1. See PATIENT LABELING for detailed information.
2. Counseling Issues:

The following points should be discussed with prospective users before prescribing progestin-only oral contraceptives:

- The necessity of taking pills at the same time every day, including throughout all bleeding episodes.
- The need to use a backup method such as condoms and spermicides for the next 48 hours whenever a progestin-only oral contraceptive is taken 3 or more hours late.
- The potential side effects of progestin-only oral contraceptives, particularly menstrual irregularities.
- The need to inform the clinician of prolonged episodes of bleeding, amenorrhea or severe abdominal pain.
- The importance of using a barrier method in addition to progestin-only oral contraceptives if a woman is at risk of contracting or transmitting STDs/HIV.

ADVERSE REACTIONS

- Menstrual irregularity is the most frequently reported side effect.
- Frequent and irregular bleeding are common, while long duration of bleeding episodes and amenorrhea are less likely.
- Headache, breast tenderness, nausea, and dizziness are increased among progestin-only oral contraceptive users in some studies.
- Androgenic side effects such as acne, hirsutism, and weight gain occur rarely.

OVERDOSAGE

There have been no reports of serious ill effects from overdosage, including ingestion by children.

DOSAGE AND ADMINISTRATION

To achieve maximum contraceptive effectiveness, Norethindrone Tablets must be taken exactly as directed. One tablet is taken every day, at the same time. Administration is continuous, with no interruption between pill packs. See PATIENT LABELING for detailed instructions.

HOW SUPPLIED

Camila™(norethindrone tablets, USP 0.35 mg) are packaged in cartons of six blister cards each containing 28 tablets. Each light pink, round, flat-faced, unscored tablet is debossed with stylizedb on one side and 715 on the other side. (NDC 54868-4814-0)

Store at controlled room temperature 15°-30°C (59°-86°F) [See USP].

REFERENCES

McCann M, and Potter L. Progestin-Only Oral Contraceptives: A Comprehensive Review. Contraception, 50:60 (Suppl. 1), December 1994.

DETAILED INFORMATION FOR THE PATIENT

This product (like all oral contraceptives) is used to prevent pregnancy. It does not protect against HIV infection (AIDS) and other sexually transmitted diseases.

INTRODUCTION

This leaflet is about birth control pills that contain one hormone, a progestin. Please read this leaflet before you begin to take your pills. It is meant to be used along with talking with your doctor or clinic.

Progestin-only pills are often called "POPs" or "the minipill." POPs have less progestin than the combined birth control pill (or "the pill") which contains both an estrogen and a progestin.

HOW EFFECTIVE ARE POPS?

About 1 in 200 POPs users will get pregnant in the first year if they all take POPs perfectly (that is, on time, every day). About 1 in 20 "typical" POPs users (including women who are late taking pills or miss pills) gets pregnant in the first year of use. The following table will help you compare the efficacy of different methods.

Table 1 Comparison of reversible contraceptive methods: Percent of women who become pregnant during the first year of use.
 | Percent of woman experiencing a pregnancy within the first year of use
Method | Average Use | Perfect Use
No contraception | 85 | 85
Spermicides | 21 | 6
Periodic abstinence | 20 | 1-9†
Withdrawal | 19 | 4
Cervical caps Given birth Never given birth | 36 18 | 26 9
Diaphragms | 18 | 6
Condoms Female Male | 21 12 | 5 3
Pills POPS Combined | 3 | 0.5 0.1
IUDs Progesterone Copper T 380A | 2 0.8 | 1.5 0.6
Injectables | 0.3 | 0.3
Implant | 0.09 | 0.09

Adapted with permission.*

*Hatcher RA, Trussel J, Stewart F, Stewart GK, Kowal D, Guest F, Cates W, Pollcar M. Contraceptive Technology 1994-1996. New York, NY: Irvington Publishers. 1994.†Depending on method (calendar, ovulation, symptom-thermal, post-ovulation).

HOW DO POPS WORK?

- They make the cervical mucus at the entrance to the womb (the uterus) too thick for the sperm to get through to the egg.
- They prevent ovulation (release of the egg from the ovary) in about half the time.
- They also affect other hormones, the fallopian tubes and the lining of the uterus.

YOU SHOULD NOT TAKE POPS

- If there is any chance you may be pregnant.
- If you have breast cancer.
- If you have bleeding between your periods which has not been diagnosed.
- If you are taking certain drugs for epilepsy (seizures) or for TB. (See USING POPS WITH OTHER MEDICINES below.)
- If you are hypersensitive or allergic to any component of this product.
- If you have liver tumors, either benign or cancerous.
- If you have acute liver disease.

RISKS OF TAKING POPS

WARNING: If you have sudden or severe pain in your lower abdomen or stomach area, you may have an ectopic pregnancy or an ovarian cyst. If this happens, you should contact your doctor or clinic immediately.

1. Ectopic Pregnancy:
  An ectopic pregnancy is a pregnancy outside the womb. Because POPs protect against pregnancy, the chance of having a pregnancy outside the womb is very low. If you do get pregnant while taking POPs, you have a slightly higher chance that the pregnancy will be ectopic than do users of some other birth control methods.
2. Ovarian Cysts:
  These cysts are small sacs of fluid in the ovary. They are more common among POP users than among users of most other birth control methods. They usually disappear without treatment and rarely cause problems.
3. Cancer of the Reproductive Organs and Breasts:
  Some studies in women who use combined oral contraceptives that contain both estrogen and a progestin have reported an increase in the risk of developing breast cancer, particularly at a younger age and apparently related to duration of use. There is insufficient data to determine whether the use of POPs similarly increases this risk.
  Some studies have found an increase in the incidence of cancer of the cervix in women who use oral contraceptives. However, this finding may be related to factors other than the use of oral contraceptives and there is insufficient data to determine whether the use of POPs increases the risk of developing cancer of the cervix.
4. Liver Tumors:
  In rare cases, combined oral contraceptives can cause benign but dangerous liver tumors. These benign liver tumors can rupture and cause fatal internal bleeding. In addition, a possible but not definite association has been found with combined oral contraceptives and liver cancers in studies in which a few women who developed these very rare cancers were found to have used combined oral contraceptives for long periods of time. There is insufficient data to determine whether POPs increase the risk of liver tumors.

SEXUALLY-TRANSMITTED DISEASES (STDS)

WARNING: POPs do not protect against getting or giving someone HIV (AIDS) or any other STD, such as chlamydia, gonorrhea, genital warts or herpes.

SIDE EFFECTS

1. Irregular Bleeding:
  The most common side effect of POPs is a change in menstrual bleeding. Your periods may be either early or late, and you may have some spotting between periods. Taking pills late or missing pills can also result in some spotting or bleeding.
2. Other Side Effects:
  Less common side effects include headaches, tender breasts, nausea and dizziness. Weight gain, acne and extra hair on your face and body have been reported, but are rare.

If you are concerned about any of these side effects, check with your doctor or clinic.

USING POPS WITH OTHER MEDICINES

Before taking a POP, inform your healthcare provider of any other medication, including over-the-counter medicine, that you may be taking.

If you are taking medicines for seizures (epilepsy) or tuberculosis (TB), tell your doctor or clinic. These medicines can make POPs less effective:

Medicines for seizures:

- Phenytoin (Dilantin®)
- Carbamazepine (Tegretol®)
- Phenobarbital

Medicine for TB:

- Rifampin (Rifampicin)

Before you begin taking any new medicines be sure your doctor or clinic knows you are taking birth control pills that contain a progestin.

HOW TO TAKE POPS

IMPORTANT POINTS TO REMEMBER

- POPs must be taken at the same time every day, so choose a time and then take the pill at that same time every day. Every time you take a pill late, and especially if you miss a pill, you are more likely to get pregnant.
- Start the next pack the day after the last pack is finished. There is no break between packs. Always have your next pack of pills ready.
- You may have some menstrual spotting between periods. Do not stop taking your pills if this happens.
- If you vomit soon after taking a pill, use a backup method (such as condom and/or spermicide) for 48 hours.
- If you want to stop taking POPs, you can do so at any time, but, if you remain sexually active and don't wish to become pregnant, be certain to use another birth control method.
- If you are not sure about how to take POPs, ask your doctor or clinic.

STARTING POPS

- It's best to take your first POP on the first day of your menstrual period.
- If you decide to take your first POP on another day, use a backup method (such as condom and/or spermicide) every time you have sex during the next 48 hours.
- If you have had a miscarriage or an abortion, you can start POPs the next day.

IF YOU ARE LATE OR MISS TAKING YOUR POPS

- If you are more than 3 hours late or you miss one or more POPs:

1. TAKE a missed pill as soon as you remember that you missed it,
2. THEN go back to taking POPs at your regular time,
3. BUT be sure to use a backup method (such as condom and/or spermicide) every time you have sex for the next 48 hours.

- If you are not sure what to do about the pills you have missed, keep taking POPs and use a backup method until you can talk to your doctor or clinic.

IF YOU ARE BREASTFEEDING

- If you are fully breastfeeding (not giving your baby any food or formula), you may start your pills 6 weeks after delivery.
- If you are partially breastfeeding (giving your baby some food or formula), you should start taking pills by 3 weeks after delivery.

IF YOU ARE SWITCHING PILLS

- If you are switching from the combined pills to POPs, take the first POP the day after you finish the last active combined pill. Do not take any of the 7 inactive pills from the combined pill pack. You should know that many women have irregular periods after switching to POPs, but this is normal and to be expected.
- If you are switching from POPs to the combined pills, take the first active combined pill on the first day of your period, even if your POPs pack is not finished.
- If you switch to another brand of POPs, start the new brand anytime.
- If you are breastfeeding, you can switch to another method of birth control at any time, except do not switch to the combined pills until you stop breastfeeding or at least until 6 months after delivery.

PREGNANCY WHILE ON THE PILL

If you become pregnant, or think you might be, stop taking POPs and contact your physician. Even though research has shown that POPs do not cause harm to the unborn baby, it is always best not to take any drugs or medicines that you don't need when you are pregnant.

You should get a pregnancy test:

- If your period is late and you took one or more pills late or missed taking them and had sex without a backup method.
- Anytime you miss 2 periods in a row.

WILL POPS AFFECT YOUR ABILITY TO GET PREGNANT LATER?

If you want to become pregnant, simply stop taking POPs. POPs will not delay your ability to get pregnant.

BREASTFEEDING

If you are breastfeeding, POPs will not affect the quality or amount of your breastmilk or the health of your nursing baby.

OVERDOSE

No serious problems have been reported when many pills were taken by accident, even by a small child, so there is usually no reason to treat an overdose.

OTHER QUESTIONS OR CONCERNS

Cigarette smoking greatly increases the possibility of suffering heart attacks and strokes. Women who use oral contraceptives are strongly advised not to smoke.

Diabetic women taking POPs do not generally require changes in the amount of insulin they are taking. However, your physician may monitor you more closely under these conditions.

If you have any questions or concerns, check with your doctor or clinic. You can also ask for the more detailed "professional package labeling" written for doctors and other healthcare providers.

HOW TO STORE YOUR POPs

Store your POPs at room temperature 15°-30°C (59°-86°F).

INSTRUCTIONS TO PATIENTS

How to Use the Camila™ Tablets Blister Card:

1. The first time you use these pills, take your first pill on the first day of your menstrual period. Pick the Days of the Week Sticker that starts the first day of your period. When you have picked the right sticker, throw away the others and place the sticker on the blister card over the pre-printed days of the week and make sure it lines up with the pills.
2. Your blister package consists of three parts, the foil pouch, wallet, and a blister card containing 28 individually sealed pills. Note that the pills are arranged in four numbered rows of 7 pills, with the pre-printed days of the week printed above them. All 28 pills are “active” birth control pills. Refer to the sample of the blister card below:
4. To remove a pill, push down on the pill with your thumb and forefinger so that the pill releases through the back of the blister card. Each day, take one pill. Always go from left to right along the row. Each new row will begin on the same day of the week.
5. Take one pill every day for 28 days, whether bleeding or not, until you have taken all the pills. It is important that you take your pill at the same time every day.
6. After you have taken all 28 pills, begin taking your pills again the next day. Be sure that the calendar day on your new package corresponds with the actual day.

MANUFACTURED BY
BARR LABORATORIES, INC.
POMONA, NY 10970

Rev AUGUST 2002

Relabeling of "Additional Barcode Label" by:
Physicians Total Care, Inc.
Tulsa, OK 74146

PRINCIPAL DISPLAY PANEL

Camila™(norethindrone tablets, USP 0.35 mg)